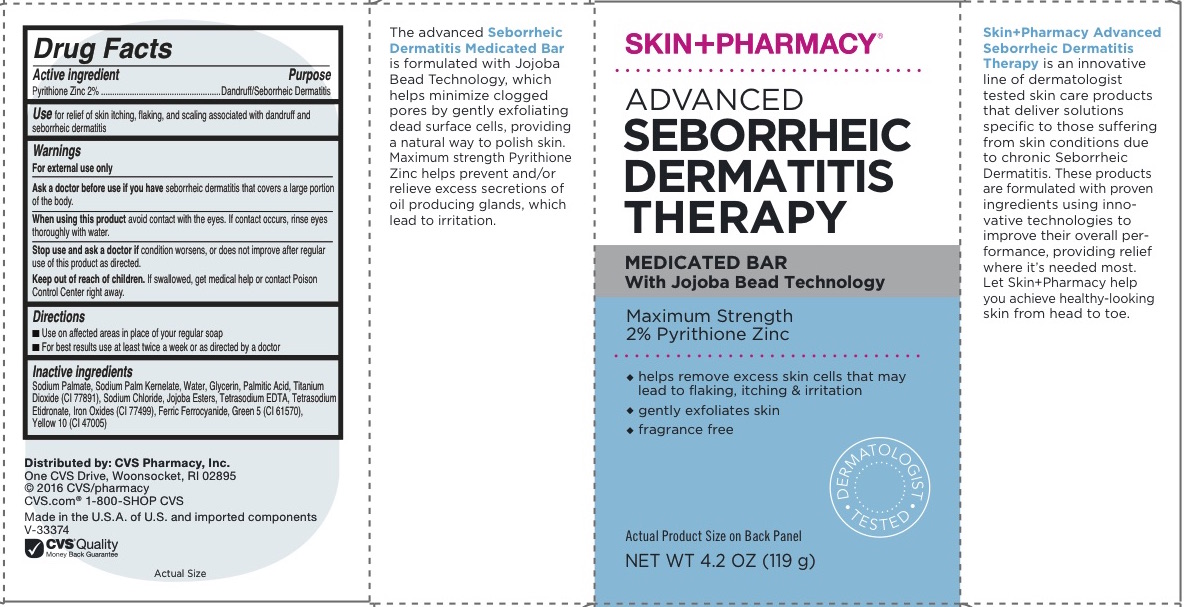 DRUG LABEL: ADVANCED SEBORRHEIC DERMATITIS THERAPY
NDC: 69842-343 | Form: SOAP
Manufacturer: CVS Pharmacy, Inc.
Category: otc | Type: HUMAN OTC DRUG LABEL
Date: 20160614

ACTIVE INGREDIENTS: PYRITHIONE ZINC 2 g/1000 g
INACTIVE INGREDIENTS: WATER; SODIUM PALM KERNELATE; SODIUM PALMATE; PALMITIC ACID; GLYCERIN; SODIUM CHLORIDE; ETIDRONATE TETRASODIUM; EDETATE SODIUM; HYDROGENATED JOJOBA OIL; TITANIUM DIOXIDE; FERRIC FERROCYANIDE; FERROUS OXIDE; D&C GREEN NO. 5; D&C YELLOW NO. 10

ADVANCED SEBORRHEIC DERMATITIS THERAPY

Active Ingredient

Pyrithione Zinc 2%

Purpose

Dandruff/Seborrheic Dermatitis

Use

For relief of skin itching, flaking, and scaling associated with dandruff and seborrheic dermatitis

Warnings

For external use only

- Keep out of the reach of children.
- If swallowed, get medical help or contact a Poison Control Center immediately.

Directions

■ Use on affected areas in place of your regular soap
■ For best results use at least twice a week or as directed by a doctor

When using this product

■ avoid contact with the eyes. If contact occurs, rinse eyes thoroughly with water.

Stop use and ask a doctor if ■ condition worsens, or does not improve after regular use of this product as directed.

Ask a doctor before use if you have seborrheic dermatitis that covers a large portion of the body.

INACTIVE INGREDIENT

Sodium Palmate, Sodium Palm Kernelate, Water, Glycerin, Palmitic Acid, Titanium Dioxide (CI 77891), Sodium Chloride, Jojoba Esters, Tetrasodium EDTA, Tetrasodium Etidronate, Iron Oxides (CI 77499), Ferric Ferrocyanide, Green 5 (CI 61570),
Yellow 10 (CI 47005)

Questions?

www.CVS.com

1-800-SHOP CVS